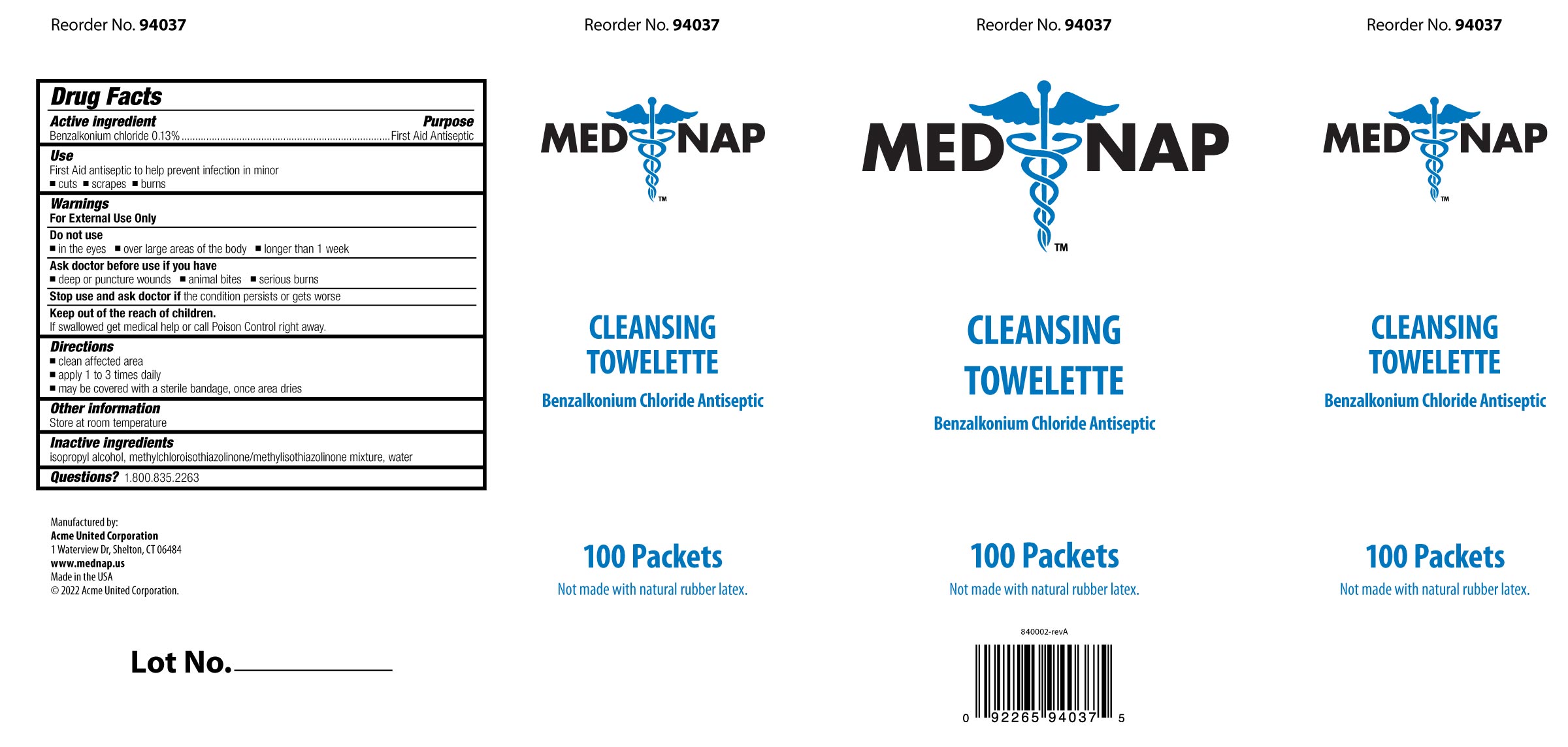 DRUG LABEL: MED NAP Cleansing Towelette
NDC: 0924-0243 | Form: LIQUID
Manufacturer: Acme United Corporation
Category: otc | Type: HUMAN OTC DRUG LABEL
Date: 20241109

ACTIVE INGREDIENTS: BENZALKONIUM CHLORIDE 0.0018 mg/1.35 mL
INACTIVE INGREDIENTS: WATER; METHYLCHLOROISOTHIAZOLINONE; METHYLISOTHIAZOLINONE; ISOPROPYL ALCOHOL

Med Nap Cleansing Towelette

Drug Facts Active Ingredient

Benzalkonium Chloride 0.13%

Purpose

First Aid antiseptic

Use:

First Aid antiseptic to help prevent infection in minor

•cuts
•scrapes
•burns

Caution:

Keep out of reach of children.

If swallowed, get medical help or contact a Poison Control center right away.

Warnings

For external use only

Do not use ▪in the eyes ▪over large areas of the body •longer than 1 week

Stop use

Stop use and ask doctor if the condition persists or gets worse

Ask doctor before use if you have

•deep or puncture wounds
•animal bites
•serious burns

Directions

To open: Tear packet open at notch, remove towelette, use it only once

•Clean affected area
•Apply 1 to 3 times daily
•May be covered with a sterile bandage, once area dries

Other Information

Store at room temperature

Inactive Ingredients

isopropyl alcohol, methylchloroisothiazolinone/methylisothiazolinone mixture, water

Questions? 1.800.835.2263

PACKAGE LABEL

Box Image